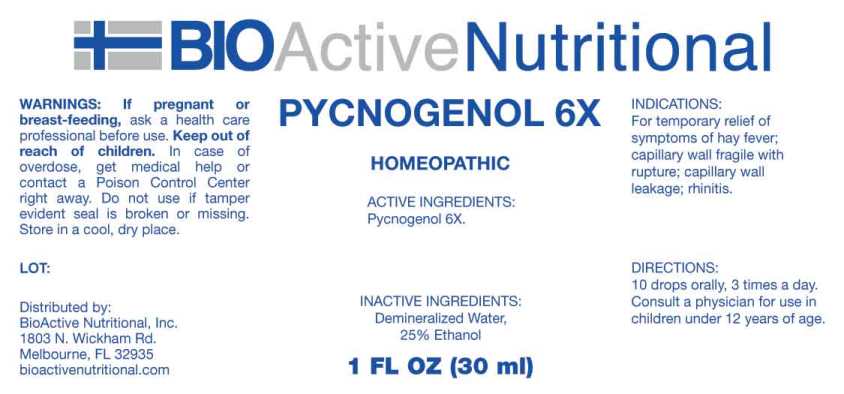 DRUG LABEL: PYCNOGENOL
NDC: 43857-0277 | Form: LIQUID
Manufacturer: BioActive Nutritional, Inc.
Category: homeopathic | Type: HUMAN OTC DRUG LABEL
Date: 20241018

ACTIVE INGREDIENTS: MARITIME PINE 6 [hp_X]/1 mL
INACTIVE INGREDIENTS: WATER; ALCOHOL

DRUG FACTS

ACTIVE INGREDIENTS:

Pycnogenol 6X.

INDICATIONS:

For temporary relief of symptoms of hay fever; capillary wall fragile with rupture; capillary wall leakage; rhinitis.

WARNINGS:

If pregnant or breast-feeding, ask a health care professional before use.

Keep out of reach of children. In case of overdose, get medical help or contact a Poison Control Center right away.

Do not use if tamper evident seal is broken or missing.

Store in cool, dry place.

Keep out of reach of children. In case of overdose, get medical help or contact a Poison Control Center right away.

DIRECTIONS:

10 drops orally, 3 times a day. Consult a physician for use in children under 12 years of age.

INDICATIONS:

For temporary relief of symptoms of hay fever; capillary wall fragile with rupture; capillary wall leakage; rhinitis.

INACTIVE INGREDIENTS:

Demineralized Water, 25% Ethanol

QUESTIONS:

Distributed by:

BioActive Nutritional, Inc.

1803 N. Wickham Rd.

Melbourne, FL 32935

bioactivenutritional.com

PACKAGE LABEL DISPLAY:

BioActive Nutritional

PYCNOGENOL 6X

HOMEOPATHIC

1 FL OZ (30 ml)